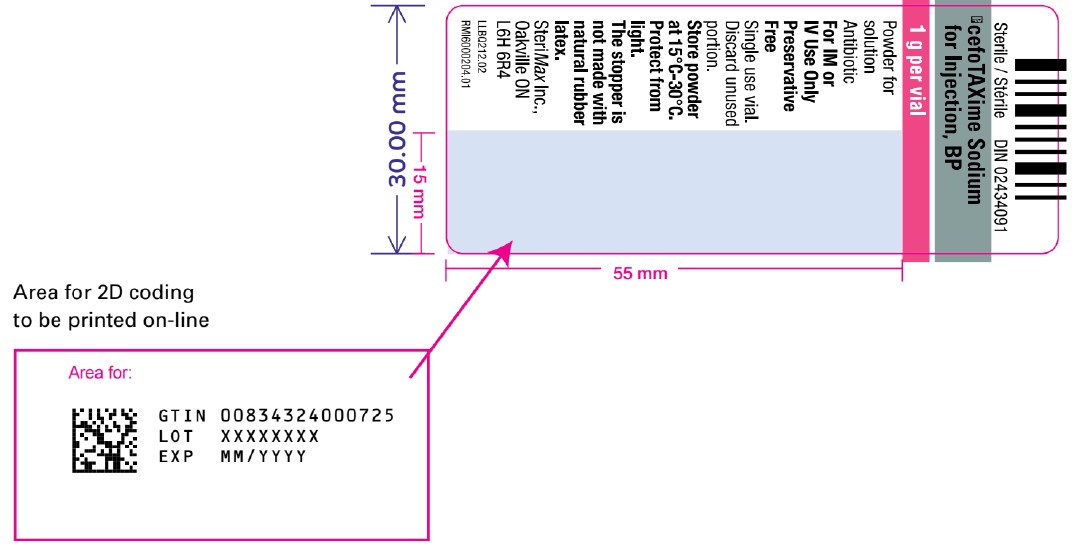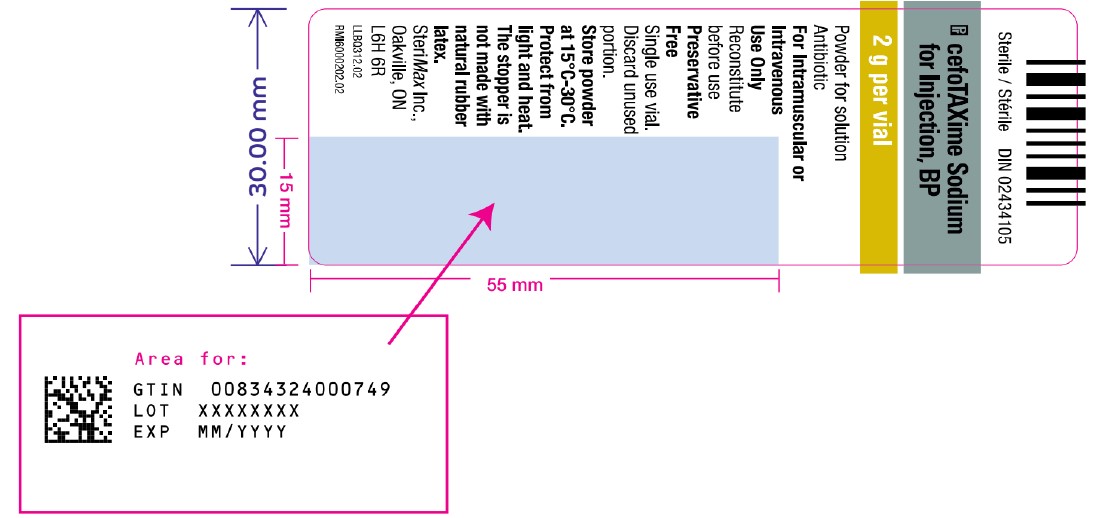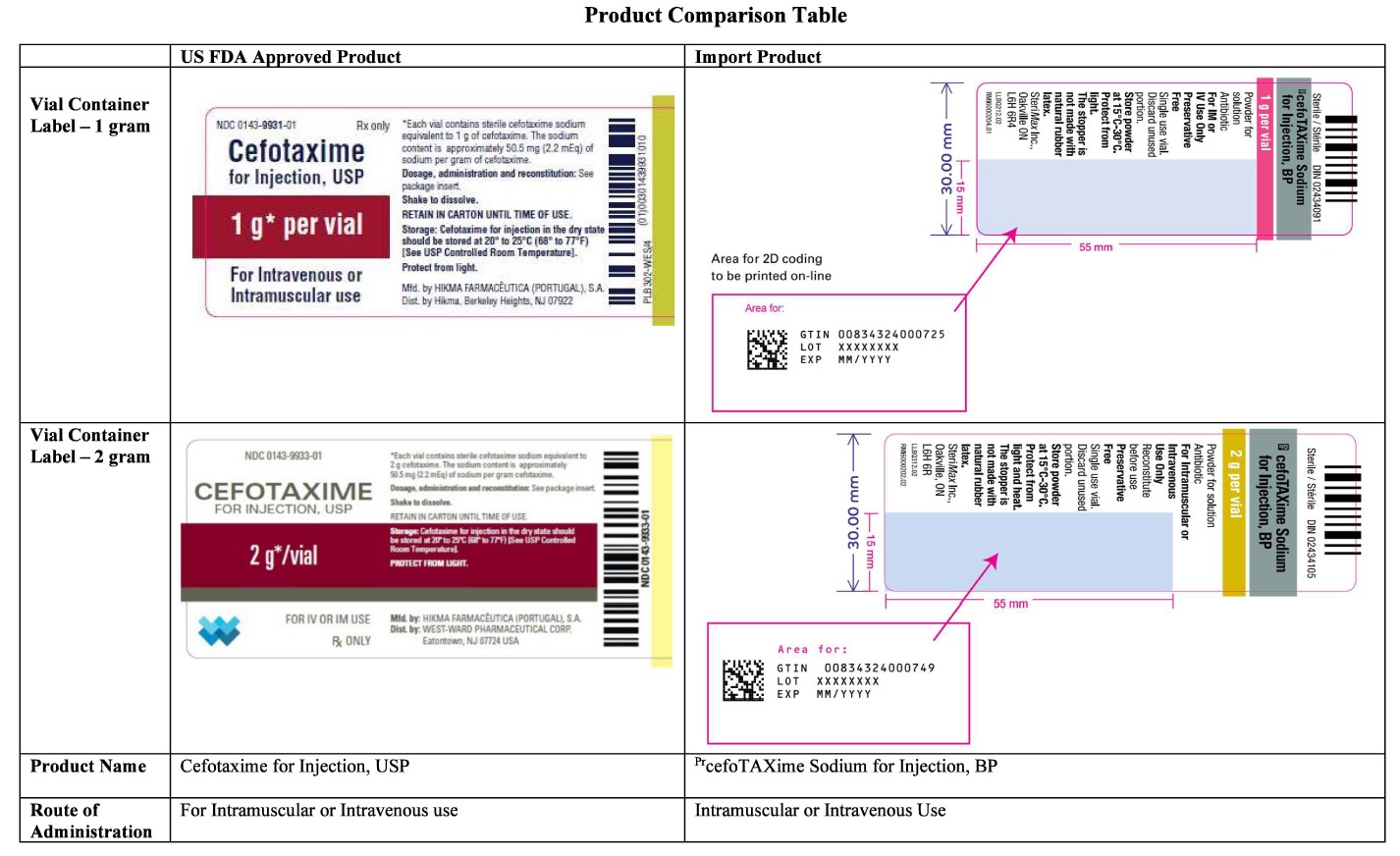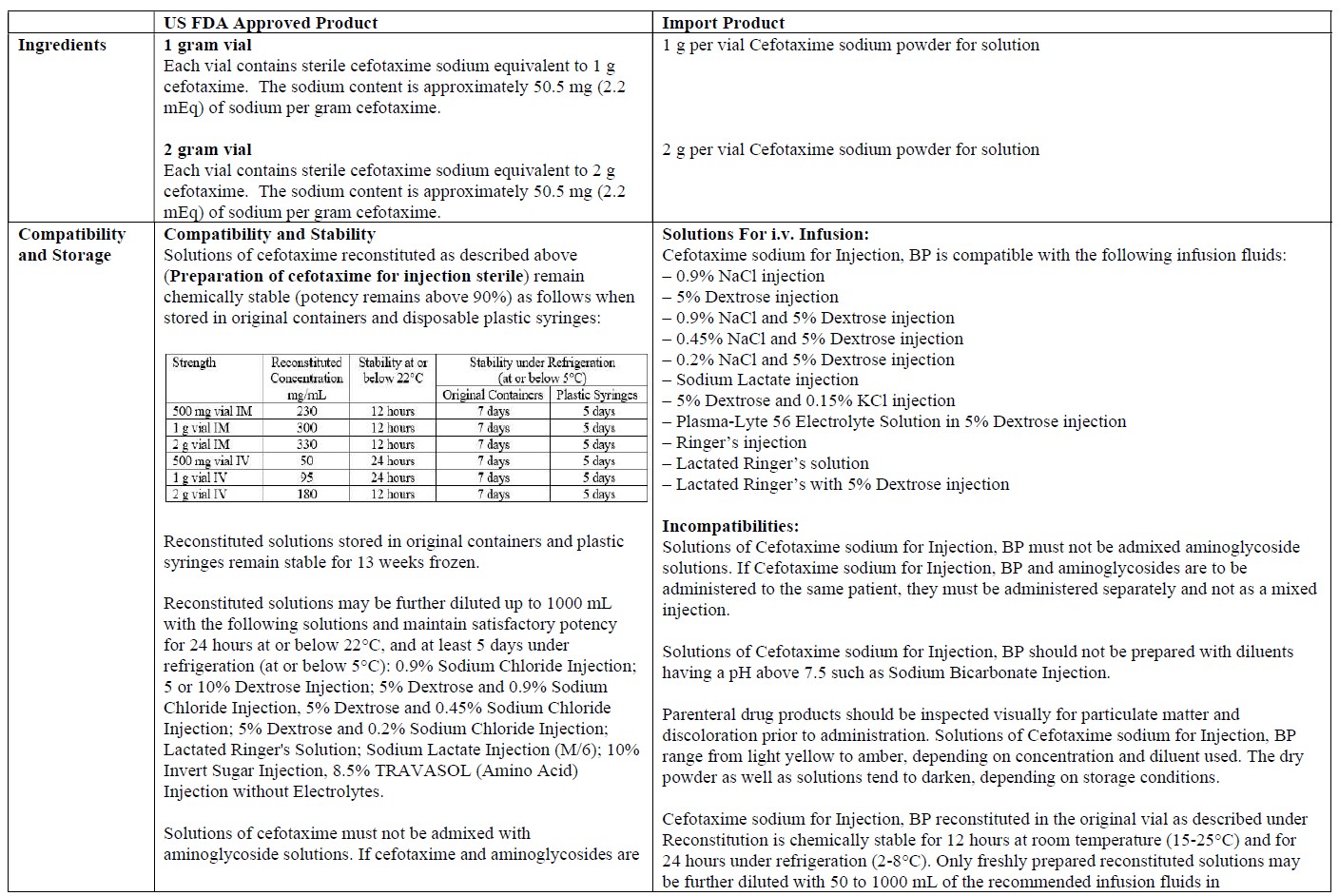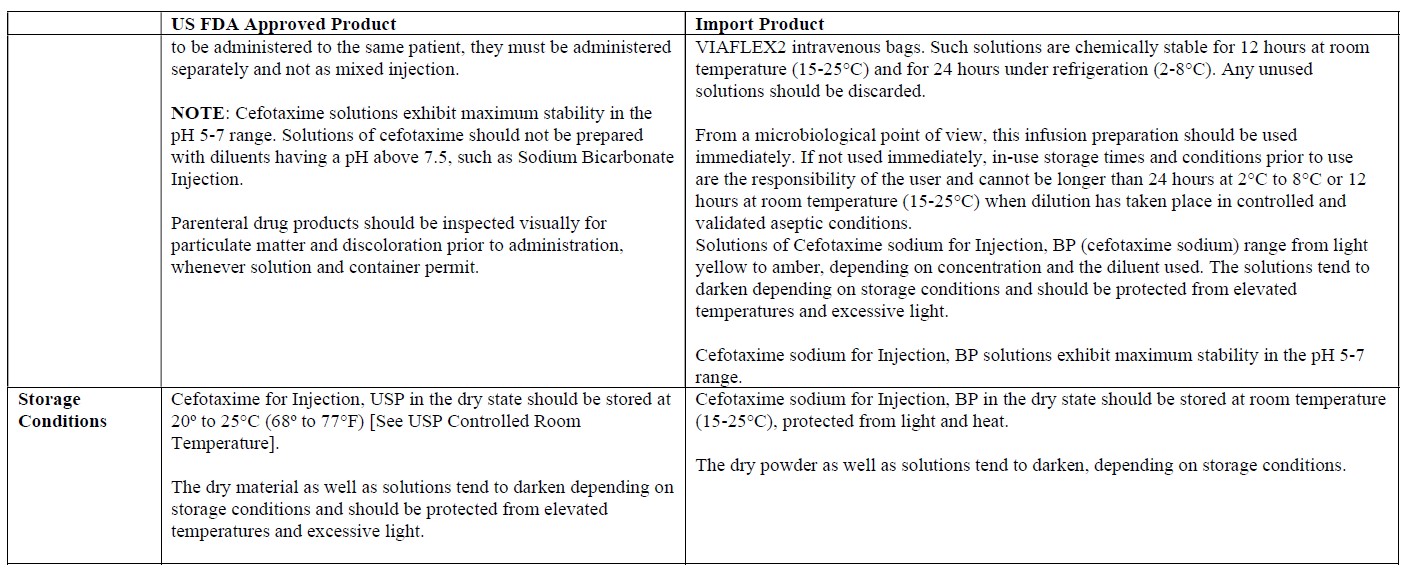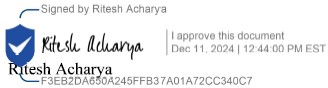 DRUG LABEL: Cefotaxime
NDC: 21586-011 | Form: POWDER, FOR SOLUTION
Manufacturer: SteriMax Inc.
Category: prescription | Type: HUMAN PRESCRIPTION DRUG LABEL
Date: 20241212

ACTIVE INGREDIENTS: CEFOTAXIME SODIUM 1 g/1 1

IMPORTANT PRESCRIBING INFORMATION

December 11, 2024

Temporary Importation of Cefotaxime for Injection to Address Drug Shortage

Dear Healthcare Professional:

Due to the current critical shortage of Cefotaxime for Injection products in the United States (U.S.) market, SteriMax Inc. (SteriMax), in conjunction with Provepharm, Inc. (Provepharm) and Direct Success, Inc. (Direct Success) is coordinating with the U.S. Food and Drug Administration (FDA) to increase the availability of the drug. SteriMax has initiated temporary importation of non-FDA approved Cefotaxime for Injection (1 g/vial, and 2 g/vial) into the U.S. market. The Cefotaxime for Injection from SteriMax is marketed in Canada and is manufactured at an FDA-inspected facility that complies with current Good Manufacturing Practice requirements.

At this time, no other entity except Provepharm or its distributor Direct Success is authorized by the FDA to import or distribute SteriMax’s Cefotaxime for Injection in the United States. FDA has not approved SteriMax’s Cefotaxime for Injection in the United States.

Effective immediately, Provepharm will distribute the following presentations of SteriMax’s Cefotaxime for Injection to address the critical shortage:

SteriMax Cefotaxime for Injection
1 g/vial (as cefotaxime sodium) | DIN: 02434091 (Canada) | NDC 21586-011-2
2 g/vial (as cefotaxime sodium) | DIN: 02434105 (Canada) | NDC 21586-012-2
Note: DIN refers to Drug Identification Number for products approved by Health Canada

The barcode on the imported product label may not register accurately on the U.S. scanning systems. Institutions should manually input the imported product information into their systems and confirm that the barcode, if scanned, provides correct information. Alternative procedures should be followed to assure that the correct drug product is being used and administered to individual patients.

In addition, the packaging of the imported product does not include serialization information. SteriMax’s Cefotaxime for Injection does not meet the Drug Supply Chain Security Act (DSCSA) requirements for the Interoperable Exchange of Information for Tracing of Human, Finished Prescription Drugs.

The vial and carton labels will display the text used and approved for marketing the products in Canada with both English and French translations. It is important to note that there are differences in the format and content of the labeling between the US approved product and SteriMax’s Cefotaxime for Injection. Please see the product comparison tables at the end of this letter.

Cefotaxime for Injection is available only by prescription in the U.S. Please refer to the package insert for the FDA-approved Cefotaxime for Injection drug product for full prescribing information.

Finally, please ensure that your staff and others in your institution who may be involved in the administration of Cefotaxime for Injection receive a copy of this letter and review the information.

If you have any questions about the information contained in this letter, any quality related problems, or questions on the use of SteriMax’s Cefotaxime for Injection, please contact SteriMax Inc. Customer Service at 1-800-881-3550.

To place an order, please contact Direct Success at Distribution@DSuccess.com or 1-877-404-3338.

Healthcare providers should report adverse events associated with the use of SteriMax’s Cefotaxime for Injection to Provepharm at 1-833-684-3234.

Adverse events or quality problems experienced with the use of this product may also be reported to the FDA’s MedWatch Adverse Event Reporting Program either online, by regular mail, or by fax:

- Complete and submit the report Online: www.fda.gov/medwatch/report.htm
- Regular mail or Fax: Download form www.fda.gov/MedWatch/getforms.htm or call 1-800-332-1088 to request a reporting form, then complete and return to the address on the pre-addressed form or submit by fax to 1-800-FDA-0178.

We remain at your disposal to answer any questions you may have about our product; and provide more information if needed.

Sincerely,

Ritesh Acharya

Chief Scientific Officer

SteriMax Inc.

Cefotaxime for Injection - 1 g per vial

Sterile/Stérile DIN 02434091

cefoTAXime Sodium for Injection, BP

1 g per vial

Powder for solution

Antibiotic

For IM or IV Use Only

Preservative Free

Single use vial. Discard unused portion.

The stopper is not made with natural rubber latex.

SteriMax Inc.

Cefotaxime for Injection - 2 g per vial

Sterile/Stérile DIN 02434105

cefoTAXime Sodium for Injection, BP

2 g per vial

Powder for solution

Antibiotic

For Intramuscular or Intravenous Use Only

Reconstitute before use

Preservative Free

Single use vial. Discard unused portion.

The stopper is not made with natural rubber latex.

SteriMax Inc.